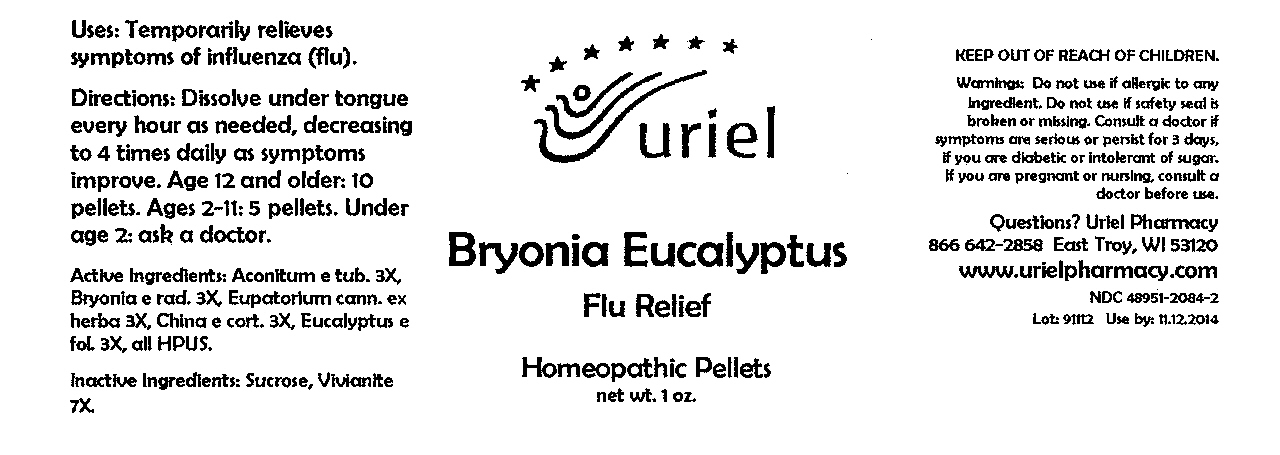 DRUG LABEL: Bryonia Eucalyptus Flu Relief
NDC: 48951-2084 | Form: PELLET
Manufacturer: Uriel Pharmacy Inc
Category: homeopathic | Type: HUMAN OTC DRUG LABEL
Date: 20091203

ACTIVE INGREDIENTS: ACONITUM NAPELLUS ROOT 3 [hp_X]/1 1; BRYONIA CRETICA SUBSP. DIOICA ROOT 3 [hp_X]/1 1; EUPATORIUM CANNABINUM WHOLE FLOWERING 3 [hp_X]/1 1; CINCHONA OFFICINALIS BARK 3 [hp_X]/1 1; EUCALYPTUS GLOBULUS LEAF 3 [hp_X]/1 1
INACTIVE INGREDIENTS: SUCROSE

Bryonia Eucalyptus Flu Relief Pellets - 1 oz.

Purpose

Uses: Temporarily relieves symptoms of influenza (flu).

Dosage & Administration

Directions: Dissolve under tongue every hour as needed, decreasing to 4 times daily as symptoms improve. Age 12 and older: 10 pellets. Ages 2-11: 5 pellets. Under age 2: ask a doctor.

OTC-Active Ingredient

Active Ingredients: Aconitum e tub. 3X, Bryonia e rad. 3X, Eupatorium cann. ex herba 3X, China e cort. 3X, Eucalyptus e fol. 3X, all HPUS.

Inactive Ingredient

Inactive Ingredient: Sucrose, Vivianite 7X.

Keep out of reach of children

Do not use section

Warnings:Do not use if allergic to any ingredient. Do not use if safety seal is broken or missing.

Ask doctor section

Consult a doctor if symptoms are serious or persist for 3 days, if you are diabetic or intolerant of sugar.

Pregnancy or breast feeding section

If you are pregnant or nursing, consult a doctor before use.

Questions section

Questions? Uriel Pharmacy

866 642-2858 East Troy, WI 53120

www.urielpharmacy.com

NDC 48951-2084-2

Principal Display Panel

Bryonia Eucalyptus

Flu Relief

Homeopathic Pellets

net wt. 1 oz.